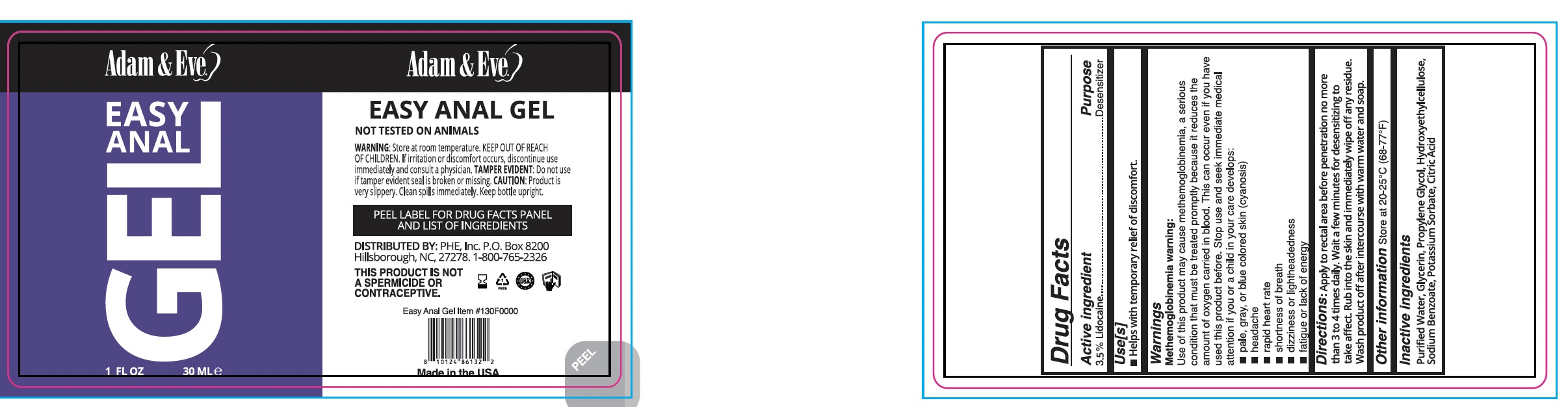 DRUG LABEL: A and E Easy Anal Gel
NDC: 87068-184 | Form: SPRAY
Manufacturer: Phe Inc
Category: otc | Type: HUMAN OTC DRUG LABEL
Date: 20251111

ACTIVE INGREDIENTS: BENZOCAINE 3.5 mg/100 mL
INACTIVE INGREDIENTS: WATER; POTASSIUM SORBATE; PROPYLENE GLYCOL; HYDROXYETHYL CELLULOSE, UNSPECIFIED; SODIUM BENZOATE; GLYCERIN; CITRIC ACID

PHE-PLP A&E A&E Easy Anal Gel

Active Ingredient(s)

Benzocaine (3.5%)

Purpose

Desensitizer

Use

Helps with temporary relief of discomfort

Warnings

Methemoglobinemia warning: Use of this product may cause methemoglobinemia, a serious condition that must be treated promptly because it reduces the amount of oxygen carried in blood. This can occur even if you have used this product before. Stop use and seek immediate medical attention if you or a child in your care develops: ■ pale, gray, or blue colored skin (cyanosis) ■ headache ■ rapid heart rate ■ shortness of breath ■ dizziness or lightheadedness ■ fatigue or lack of energy

KEEP OUT OF REACH OF CHILDREN

Keep out of reach of childeren. Contact a Poison Control Center: This is the emergency contact for accidental overdose or ingestion

Directions

Apply to rectal area before penetration, no more than 3–4 times daily. Wait a few minutes for desensitizing to take effect. Rub into the skin and wipe off any residue. Wash product off after intercourse with warm water and soap.

Other information

Store at 20-25°C (68-77°F)

Inactive ingredients

Purified Water, Glycerin, Propylene Glycol, Hydroxyethylcellulose, Sodium Benzoate, Potassium Sorbate, Citric Acid.